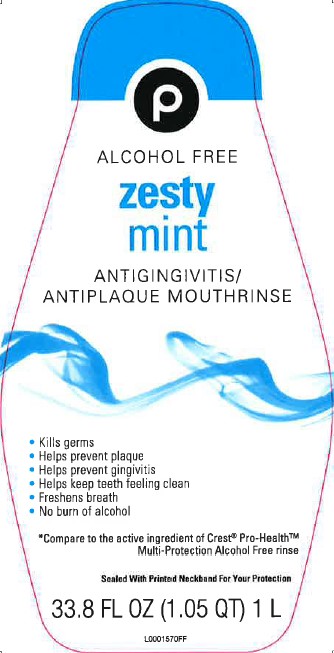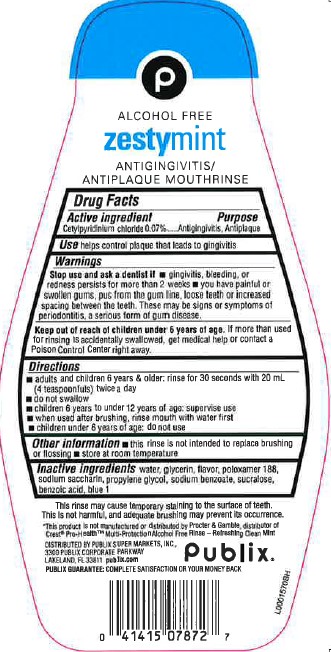 DRUG LABEL: Zestymint Antiseptic
NDC: 56062-299 | Form: MOUTHWASH
Manufacturer: Publix Super Markets, Inc.
Category: otc | Type: HUMAN OTC DRUG LABEL
Date: 20260205

ACTIVE INGREDIENTS: CETYLPYRIDINIUM CHLORIDE 0.7 mg/1 mL
INACTIVE INGREDIENTS: WATER; GLYCERIN; POLOXAMER 188; SACCHARIN SODIUM; PROPYLENE GLYCOL; SODIUM BENZOATE; SUCRALOSE; BENZOIC ACID; FD&C BLUE NO. 1

Publix 299.005/299AL
Multi Action Alcohol Free Antiseptic Rinse w/CPC

Claims

P

ALCOHOL FREE

zesty mint

ANTIGINGIVITIS/ANTIPLAQUE MOUTHRINSE

Active ingredient

Cetylpyridinium chloride 0.07%

Purpose

Antigingivitis, Antiplaque

Use

helps control plaque that leads to gingivitis

Warnings

for this product

Stop use and ask a dentist if

- gingivitis, bleeding, or redness persists for more than 2 weeks
- you have painful or swollen gums, pus from the gum line, loose teeth or increased spacing between the teeth. These may be signs or symptoms of periodontitis, a serious form of gum disease.

Keep out of reach of children under 6 years of age.

If more than used for rinsing is accidentally swallowed, get medical help or contact a Poison Control Center right away.

Directions

- adults and children 6 years & older: rinse for 30 seconds with 20 mL (4 teaspoonfuls) twice a day
- do not swallow
- children 6 years to under 12 years of age: supervise use
- when used after brushing, rinse mouth with water first
- children under 6 years of age: do not use

Other information

- this rinse is not intended to replace brushing or flossing
- store at room temperature

Inactive ingredients

water, glycerin, flavor, poloxamer 188, sodium saccharin, propylene glycol, sodium benzoate, sucralose, benzoic acid, blue 1

Disclaimers

This rinse may cause temporary staining to the surface of teeth.

This is not harmful, and adequate brushing may prevent its occurence.

*This product is not manufactured or distributed by Procter & Gamble, distributor of Crest®Pro-Health™ Multi-Protection Alcohol Free Rinse - Refreshing Clean Mint.

ADVERSE REACTION

DISTRIBUTED BY PUBLIX SUPER MARKETS, INC.

3300 PUBLIX CORPORATE PARKWAY

LAKELAND, FL 33811 publix.com

Publix Guarantee: Complete Satisfaction or your money back

Publix

principal display panel

P

ALCOHOL FREE

ZESTY MINT

ANTIGINGIVITIS/ANTISEPTIC MOUTHRINSE

- kills germs
- helps prevent plaque
- helps prevent gingivitis
- helps keep teeth feeling clean
- freshens breath
- no burn of alcohol

*COMPARE TO THE ACTIVE INGREDIENT OF CREST®PRO-HEALTH™ MULTI-PROTECTION ALCOHOL FREE RINSE

Sealed With Printed Neckband For Your Protection

33.8 FL OZ (1.05 QT) 1 L